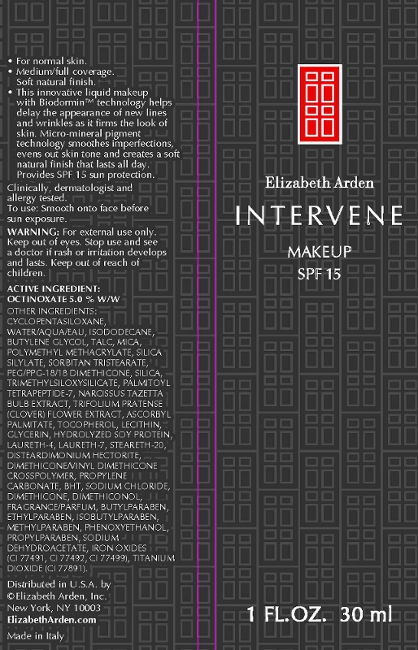 DRUG LABEL: Intervene Makeup SPF 15 Soft Bronze
NDC: 67938-1086 | Form: CREAM
Manufacturer: Elizabeth Arden, Inc
Category: otc | Type: HUMAN OTC DRUG LABEL
Date: 20110113

ACTIVE INGREDIENTS: OCTINOXATE 1.5 mL/30 mL
INACTIVE INGREDIENTS: WATER; ISODODECANE; BUTYLENE GLYCOL; TALC; SORBITAN TRISTEARATE; SILICON DIOXIDE; MICA; PHENOXYETHANOL; DIMETHICONE; SODIUM CHLORIDE; GLYCERIN; PROPYLENE CARBONATE; LAURETH-7; SODIUM DEHYDROACETATE; METHYLPARABEN; ETHYLPARABEN; BUTYLPARABEN; NARCISSUS TAZETTA BULB; PROPYLPARABEN; ISOBUTYLPARABEN; LAURETH-4; ALPHA-TOCOPHEROL; ASCORBYL PALMITATE; STEARETH-20; BUTYLATED HYDROXYTOLUENE; TRIFOLIUM PRATENSE FLOWER; PALMITOYL TETRAPEPTIDE-7

BC1086

DESCRIPTION

For normal skin. Medium/full coverage. Soft natural finish. This innovative liquid makeup with Biodormin technology helps delay the appearance of new lines and wrinkles as it firms the look of skin. Micro-mineral pigment technology smoothes imperfections, evens out skin tone and creates a soft natural finish that lasts all day. Provides SPF 15 sun protection. Clinitcally, dermatologist, and allergy tested.

INDICATIONS AND USAGE

To Use: Smooth on to face before sun exposure.

WARNINGS

Warning: For external use only. Keep out of eyes. Stop use and see a doctor if rash or irritation develops and lasts. Keep out of reach of children.

OTC - ACTIVE INGREDIENT

Active Ingredient: Octinoxate 5% w/w.

INACTIVE INGREDIENT

Other Ingredients: Cyclopentasiloxane, Water/Aqua/Eau, Isododecane, Butylene Glycol, Ethylhexyl Methoxycinnamate, Talc, Mica, Polymethyl Methacrylate, Silica Silylate, Sorbitan Tristearate, PEG/PPG-18/18 Dimethicone, Silica, Trimethylsiloxysilicate, Palmitoyl Tetrapeptide-7, Narcissus Tazetta Bulb Extract, Trifolium Pratense (Clover) Flower Extract, Ascorbyl Plamitate, Tocopherol, Lecithin, Clycerin, Hydolyzed Soy Protein, Laureth-4, Laureth-7, Steareth-20, Disteardimonium Hectorite, Deimethicone/Vinyl Dimethicone Crosspolymer, Propylene Carbonate, BHT, Sodium Chloride, Dimethicone, Dimethiconol, Fragrance/Parfum, Butylparaben, Ethylparaben, Isobutylparaben, Methylparaben, Phenoxyethanol, Propylparaben, Sodium Dehydroacetate, Iron Oxides (CI 77491, CI 77492, CI 77499), Titanium Dioxide (CI77891).

DOSAGE & ADMINISTRATION

Smooth on to face.

KEEP OUT OF REACH OF CHILDREN

OTC - PURPOSE

Provides SPF 15 sun protection.

OTC - WHEN USING

Keep out of eyes.